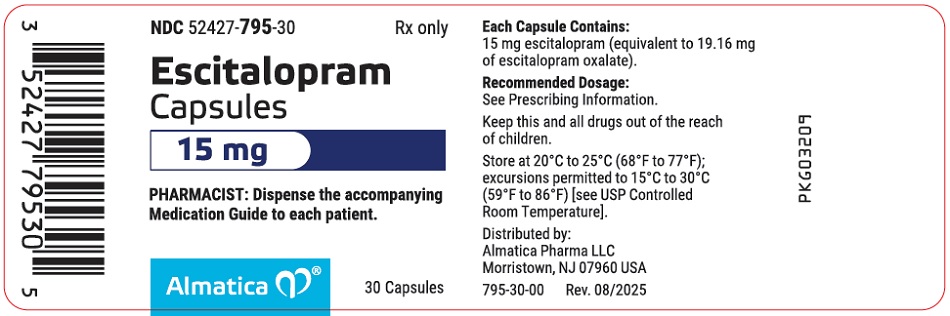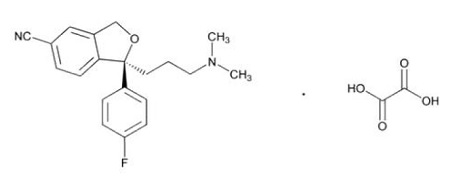 DRUG LABEL: escitalopram
NDC: 52427-795 | Form: CAPSULE
Manufacturer: Almatica Pharma LLC
Category: prescription | Type: HUMAN PRESCRIPTION DRUG LABEL
Date: 20250831

ACTIVE INGREDIENTS: ESCITALOPRAM OXALATE 15 mg/1 1
INACTIVE INGREDIENTS: CROSCARMELLOSE SODIUM; COPOVIDONE K25-31; FD&C BLUE NO. 1; FD&C RED NO. 40; GELATIN, UNSPECIFIED; MAGNESIUM STEARATE; MICROCRYSTALLINE CELLULOSE; SODIUM LAURYL SULFATE; TALC; TITANIUM DIOXIDE

HIGHLIGHTS OF PRESCRIBING INFORMATION

These highlights do not include all the information needed to use ESCITALOPRAM CAPSULES safely and effectively. See full prescribing information for ESCITALOPRAM CAPSULES.
ESCITALOPRAM capsules, for oral use
Initial U.S. Approval: 2002

WARNING: SUICIDAL THOUGHTS AND BEHAVIORS

See full prescribing information for complete boxed warning.

Increased risk of suicidal thoughts and behavior in pediatric and young adult patients taking antidepressants. Closely monitor all antidepressant-treated patients for clinical worsening and emergence of suicidal thoughts and behaviors. (5.1)

1 INDICATIONS AND USAGE

Escitalopram Capsules are a selective serotonin reuptake inhibitor (SSRI) indicated for the treatment of: (1)

- Major depressive disorder in adults younger than 65 years of age and pediatric patients 12 years of age and older
- Generalized anxiety disorder in adults younger than 65 years of age

2 DOSAGE AND ADMINISTRATION

- Escitalopram Capsules are only available in a 15 mg strength (2.1)
- Use another escitalopram product for dosage initiation, titration, dosages other than 15 mg once daily, and for discontinuation (2.1)
- Escitalopram Capsules are not indicated in geriatric patients and not recommended in patients with hepatic impairment (2.1)
- Recommended starting dosage is 10 mg orally once daily of another escitalopram product. Based on response and tolerability, may increase to the maximum recommended dosage of 20 mg once daily of another escitalopram product (2.2, 2.3)
- Escitalopram Capsules 15 mg orally once daily may be initiated in patients experiencing unfavorable tolerability to a 20 mg escitalopram dosage (2.2, 2.3)
- Administer orally once daily with or without food. Swallow capsules whole (2.4)
- When discontinuing, reduce dosage gradually using another escitalopram product (2.7, 5.3)

3 DOSAGE FORMS AND STRENGTHS

Capsules: 15 mg of escitalopram (3)

4 CONTRAINDICATIONS

- Concomitant use of monoamine oxidase inhibitor (MAOI) or within 14 days of stopping an MAOI (4, 5.2, 7)
- Concomitant use of pimozide (4, 7)
- Known hypersensitivity to escitalopram or citalopram or any inactive ingredient in Escitalopram Capsules (4)

5 WARNINGS AND PRECAUTIONS

- Serotonin Syndrome: Increased risk when co-administered with other serotonergic agents but also when taken alone. If it occurs, discontinue Escitalopram Capsules and serotonergic agents and initiate supportive treatment (4, 5.2, 7)
- Discontinuation Syndrome: When discontinuing reduce dosage gradually whenever possible, and monitor for discontinuation symptoms (2.7, 5.3)
- Seizures: Use with caution in patients with a history of seizure (5.4)
- Activation of Mania/Hypomania: Screen patients for bipolar disorder (5.5)
- Hyponatremia: Can occur in association with syndrome of inappropriate antidiuretic hormone secretion (5.6)
- Increased Risk of Bleeding: Concomitant use of nonsteroidal anti-inflammatory drugs, aspirin, other antiplatelet drugs, warfarin and other anticoagulants may increase risk (5.7, 7)
- Interference with Cognitive and Motor Performance: Use caution when operating machinery (5.8)
- Angle Closure Glaucoma: Avoid use of antidepressants, including Escitalopram Capsules, in patients with untreated anatomically narrow angles (5.9)
- Use in Patients with Concomitant Illness: Use caution in patients with diseases or conditions that produce altered metabolism or hemodynamic responses (5.10)
- Sexual Dysfunction: Escitalopram Capsules may cause symptoms of sexual dysfunction (5.11)

6 ADVERSE REACTIONS

Most common adverse reactions (≥ 5% and at least twice the incidence of placebo) are: insomnia, ejaculation disorder (primarily ejaculatory delay), nausea, increased sweating, fatigue and somnolence, decreased libido, and anorgasmia (6.1)

To report SUSPECTED ADVERSE REACTIONS, contact Almatica Pharma LLC at 1-877-447-7979 or FDA at 1-800-FDA-1088 or www.fda.gov/medwatch.

7 DRUG INTERACTIONS

See full prescribing information for clinically significant drug interactions (7)

8 USE IN SPECIFIC POPULATIONS

Pregnancy: SSRI use, particularly late in pregnancy, may increase the risk for persistent pulmonary hypertension and symptoms of poor adaptation (respiratory distress, temperature instability, feeding difficulties, hypotonia, tremor, irritability) in the neonate (8.1)

Additional pediatric use information is approved for AbbVie Inc.’s LEXAPRO (escitalopram) tablets and LEXAPRO (escitalopram) oral solution. However, due to AbbVie Inc.’s marketing exclusivity rights, this drug product is not labeled with that information.

FULL PRESCRIBING INFORMATION

WARNING: SUICIDAL THOUGHTS AND BEHAVIORS

Antidepressants increased the risk of suicidal thoughts and behaviors in pediatric and young adult patients in short-term studies. Closely monitor all antidepressant-treated patients for clinical worsening, and for emergence of suicidal thoughts and behaviors [see Warnings and Precautions (5.1)].

1 INDICATIONS AND USAGE

Escitalopram Capsules are indicated for the treatment of:

- Major depressive disorder (MDD) in adults younger than 65 years of age [see Dosage and Administration (2.1)] and pediatric patients 12 years of age and older.
- Generalized anxiety disorder (GAD) in adults younger than 65 years of age [see Dosage and Administration (2.1)].

Additional pediatric use information is approved for AbbVie Inc.’s LEXAPRO (escitalopram) tablets and LEXAPRO (escitalopram) oral solution. However, due to AbbVie Inc.’s marketing exclusivity rights, this drug product is not labeled with that information.

2 DOSAGE AND ADMINISTRATION

2.1 Important Dosage Information

Escitalopram Capsules are only available in a 15 mg strength. Use another escitalopram product for initial dosage, dosage titration, administration of dosages other than 15 mg once daily, and to taper during discontinuation [see Dosage and Administration (2.2, 2.3, 2.7)]. Refer to the Prescribing Information of other escitalopram products for the recommended dosage for those products.

Escitalopram Capsules may be initiated in patients experiencing unfavorable tolerability to a 20 mg escitalopram dosage [see Dosage and Administration (2.2, 2.3)].

Escitalopram Capsules are not indicated in geriatric patients. Avoid use of Escitalopram Capsules in geriatric patients because the recommended dosage in these patients cannot be achieved with the Escitalopram Capsules 15 mg strength [see Use in Specific Populations (8.5)].

Escitalopram Capsules are not recommended in patients with hepatic impairment because the recommended dosage in such patients cannot be achieved with the Escitalopram Capsules 15 mg strength [see Use in Specific Populations (8.6)].

2.2 Recommended Dosage for Major Depressive Disorder

The recommended starting dosage of escitalopram for MDD in adults younger than 65 years of age and pediatric patients 12 years of age and older is 10 mg orally once daily. Use another escitalopram product for dosage initiation.

Based on clinical response and tolerability, the dosage may be increased to the maximum recommended dosage of 20 mg once daily of another escitalopram product after at least 1 week in adults younger than 65 years of age and after 3 weeks in pediatric patients 12 years of age and older. Escitalopram Capsules 15 mg orally once daily may be initiated in patients experiencing unfavorable tolerability to a 20 mg escitalopram dosage.

2.3 Recommended Dosage for Generalized Anxiety Disorder

The recommended starting dosage of escitalopram for GAD in adults younger than 65 years of age is 10 mg orally once daily. Use another escitalopram product for dosage initiation.

Based on clinical response and tolerability, the dosage may be increased to the maximum recommended dosage of 20 mg once daily of another escitalopram product after at least 1 week in adults younger than 65 years of age. Escitalopram Capsules 15 mg orally once daily may be initiated in patients experiencing unfavorable tolerability to a 20 mg escitalopram dosage.

Additional pediatric use information is approved for AbbVie Inc.’s LEXAPRO (escitalopram) tablets and LEXAPRO (escitalopram) oral solution. However, due to AbbVie Inc. ’s marketing exclusivity rights, this drug product is not labeled with that information.

2.4 Administration Information

Administer Escitalopram Capsules orally once daily, in the morning or evening, with or without food [see Clinical Pharmacology (12.3)]. Swallow capsules whole; do not open, crush, or chew.

2.5 Screen for Bipolar Disorder Prior to Starting Escitalopram Capsules

Prior to initiating treatment with Escitalopram Capsules or another antidepressant, screen patients for a personal family history of bipolar disorder, mania, or hypomania [see Warnings and Precautions (5.5)].

2.6 Switching Patients to or from a Monoamine Oxidase Inhibitor Antidepressant

At least 14 days must elapse between discontinuation of a monoamine oxidase inhibitor (MAOI) antidepressant and initiation of Escitalopram Capsules. In addition, at least 14 days must elapse after stopping Escitalopram Capsules before starting an MAOI antidepressant [see Contraindications (4), Warnings and Precautions (5.2)].

2.7 Discontinuing Treatment with Escitalopram Capsules

Adverse reactions may occur upon discontinuation of Escitalopram Capsules [see Warnings and Precautions (5.3)]. Gradually reduce the dosage rather than stopping Escitalopram Capsules abruptly whenever possible. Given that 15 mg is the only available dosage strength of Escitalopram Capsules, gradual dosage reduction will require the use of another escitalopram product.

3 DOSAGE FORMS AND STRENGTHS

Capsules: 15 mg of escitalopram available as hard shell gelatin capsules, with “ALM” printed axially on the light blue opaque cap and “795” printed axially on the blue opaque body. All printing is in black ink.

4 CONTRAINDICATIONS

Escitalopram Capsules are contraindicated in patients:

- Taking, or within 14 days of stopping, MAOIs, including linezolid or intravenous methylene blue, because of an increased risk of serotonin syndrome [see Dosage and Administration (2.6), Warnings and Precautions (5.2), Drug Interactions (7)].
- Taking pimozide because of the risk of QT prolongation [see Drug Interactions (7)].
- With known hypersensitivity to escitalopram or citalopram or any of the inactive ingredients in Escitalopram Capsules.

5 WARNINGS AND PRECAUTIONS

5.1 Suicidal Thoughts and Behaviors in Adolescents and Young Adults

In pooled analyses of placebo-controlled trials of antidepressant drugs (SSRIs and other antidepressant classes) that included approximately 77,000 adult patients and 4,500 pediatric patients, the incidence of suicidal thoughts and behaviors in the antidepressant-treated patients age 24 years and younger was greater than in placebo-treated patients. There was considerable variation in risk of suicidal thoughts and behaviors among drugs, but there was an increased risk identified in young patients for most drugs studied. There were differences in absolute risk of suicidal thoughts and behaviors across the different indications, with the highest incidence in patients with MDD. The drug-placebo differences in the number of cases of suicidal thoughts and behaviors per 1000 patients treated are provided in Table 1.

Table 1: Risk Differences of the Number of Patients of Suicidal Thoughts and Behaviors in the Pooled Placebo-Controlled Trials of Antidepressants in Pediatric and Adult Patients
Age Range | Drug-Placebo Difference in Number of Patients of Suicidal Thoughts and Behaviors per 1000 Patients Treated
 | Increases Compared to Placebo
<18 years old | 14 additional patients
18 to 24 years old | 5 additional patients
 | Decreases Compared to Placebo
25 to 64 years old | 1 fewer patient
≥65 years old | 6 fewer patients

It is unknown whether the risk of suicidal thoughts and behaviors in children, adolescents, and young adults extends to longer-term use, i.e., beyond four months. However, there is substantial evidence from placebo-controlled maintenance trials in adults with MDD that antidepressants delay the recurrence of depression and that depression itself is a risk factor for suicidal thoughts and behaviors.

Monitor all antidepressant-treated patients for any indication for clinical worsening and emergence of suicidal thoughts and behaviors, especially during the initial few months of drug therapy, and at times of dosage changes. Counsel family members or caregivers of patients to monitor for changes in behavior and to alert the healthcare provider. Consider changing the therapeutic regimen, including possibly discontinuing Escitalopram Capsules, in patients whose depression is persistently worse, or who are experiencing emergent suicidal thoughts or behaviors.

5.2 Serotonin Syndrome

SSRIs, including Escitalopram Capsules, can precipitate serotonin syndrome, a potentially life-threatening condition. The risk is increased with concomitant use of other serotonergic drugs (including triptans, tricyclic antidepressants, fentanyl, meperidine, methadone, lithium, tramadol, tryptophan, buspirone, amphetamines, and St. John’s Wort) and with drugs that impair metabolism of serotonin, i.e., MAOIs [see Contraindications (4), Drug Interactions (7)]. Serotonin syndrome can also occur when these drugs are used alone.

Serotonin syndrome symptoms may include mental status changes (e.g., agitation, hallucinations, delirium, and coma), autonomic instability (e.g., tachycardia, labile blood pressure, dizziness, diaphoresis, flushing, hyperthermia), neuromuscular symptoms (e.g., tremor, rigidity, myoclonus, hyperreflexia, incoordination) seizures, and/or gastrointestinal symptoms (e.g., nausea, vomiting, diarrhea).

The concomitant use of Escitalopram Capsules with MAOIs is contraindicated. In addition, do not initiate Escitalopram Capsules in a patient who is being treated with MAOIs such as linezolid or intravenous methylene blue. No reports involved the administration of methylene blue by other routes (such as oral tablets or local tissue injection). If it is necessary to initiate treatment with an MAOI such as linezolid or intravenous methylene blue in a patient taking Escitalopram Capsules, discontinue Escitalopram Capsules before initiating treatment with the MAOI [see Dosage and Administration (2.6), Contraindications (4)].

Monitor all patients taking Escitalopram Capsules for the emergence of serotonin syndrome. Discontinue treatment with Escitalopram Capsules and any concomitant serotonergic agents immediately if the above symptoms occur, and initiate supportive symptomatic treatment. If concomitant use of Escitalopram Capsules with other serotonergic drugs is clinically warranted, inform patients of the increased risk for serotonin syndrome and monitor for symptoms.

5.3 Discontinuation Syndrome

Adverse reactions after discontinuation of serotonergic antidepressants, particularly after abrupt discontinuation, include: nausea, sweating, dysphoric mood, irritability, agitation, dizziness, sensory disturbances (e.g., paresthesia, such as electric shock sensations), tremor, anxiety, confusion, headache, lethargy, emotional lability, insomnia, hypomania, tinnitus, and seizures. A gradual reduction in dosage rather than abrupt cessation is recommended whenever possible [see Dosage and Administration (2.7)].

5.4 Seizures

Although anticonvulsant effects of racemic citalopram have been observed in animal studies, Escitalopram Capsules have not been systematically evaluated in patients with a seizure disorder. Patients with a seizure disorder were excluded from premarketing clinical studies. In clinical trials of another escitalopram product, cases of convulsion have been reported in association with escitalopram treatment. Like other drugs effective in the treatment of major depressive disorder, Escitalopram Capsules should be introduced with care in patients with a history of seizure disorder.

5.5 Activation of Mania or Hypomania

In patients with bipolar disorder, treating a depressive episode with Escitalopram Capsules or another antidepressant may precipitate a mixed/manic episode. In controlled trials of another escitalopram product in major depressive disorder, activation of mania/hypomania was reported in 0.1% of patients treated with escitalopram and none of the patients treated with placebo. One additional case of hypomania has been reported in association with escitalopram treatment. Activation of mania/hypomania has also been reported in a small proportion of patients with major affective disorders treated with racemic citalopram and other marketed drugs effective in the treatment of major depressive disorder.

Prior to initiating treatment with Escitalopram Capsules, screen patients for any personal or family history of bipolar disorder, mania, or hypomania [see Dosage and Administration (2.3)].

5.6 Hyponatremia

Hyponatremia may occur as a result of treatment with SSRIs, including Escitalopram Capsules. In many cases, this hyponatremia appears to be the result of the syndrome of inappropriate antidiuretic hormone secretion (SIADH) and was reversible when escitalopram was discontinued. Cases with serum sodium lower than 110 mmol/L have been reported with another escitalopram product. Geriatric patients may be at greater risk of developing hyponatremia with SSRIs and SNRIs (Escitalopram Capsules are not indicated in geriatric patients) [see Use in Specific Populations (8.5)]. Also, patients taking diuretics or who are otherwise volume depleted may be at greater risk. Consider discontinuing Escitalopram Capsules in patients with symptomatic hyponatremia and institute appropriate medical intervention.

Signs and symptoms of hyponatremia include headache, difficulty concentrating, memory impairment, confusion, weakness, and unsteadiness, which may lead to falls. Signs and symptoms associated with more severe and/or acute cases have included hallucination, syncope, seizure, coma, respiratory arrest, and death.

5.7 Increased Risk of Bleeding

Drugs that interfere with serotonin reuptake inhibition, including Escitalopram Capsules, increase the risk of bleeding events. Concomitant use of aspirin, nonsteroidal anti-inflammatory drugs (NSAIDs), other antiplatelet drugs, warfarin, and other anticoagulants may add to the risk. Case reports and epidemiological studies (case-control and cohort design) have demonstrated an association between use of drugs that interfere with serotonin reuptake and the occurrence of gastrointestinal bleeding. Based on data from the published observational studies, exposure to SSRIs, particularly in the month before delivery, has been associated with a less than 2-fold increase in the risk of postpartum hemorrhage [see Use in Specific Populations (8.1)]. Bleeding events related to drugs that interfere with serotonin reuptake have ranged from ecchymoses, hematomas, epistaxis, and petechiae to life-threatening hemorrhages.

Inform patients about the increased risk of bleeding associated with the concomitant use of Escitalopram Capsules and antiplatelet agents or anticoagulants. For patients taking warfarin, carefully monitor the international normalized ratio [see Drug Interactions (7)].

5.8 Interference with Cognitive and Motor Performance

In a study of another escitalopram product in normal volunteers, escitalopram 10 mg daily did not produce impairment of intellectual function or psychomotor performance. Because any psychoactive drug may impair judgment, thinking, or motor skills, however, patients should be cautioned about operating hazardous machinery, including automobiles, until they are reasonably certain that Escitalopram Capsules do not affect their ability to engage in such activities.

5.9 Angle Closure Glaucoma

The pupillary dilation that occurs following use of many antidepressant drugs, including Escitalopram Capsules, may trigger an angle closure attack in a patient with anatomically narrow angles who does not have a patent iridectomy. Avoid use of antidepressants, including Escitalopram Capsules, in patients with untreated anatomically narrow angles.

Pre-existing glaucoma is almost always open-angle glaucoma because angle closure glaucoma, when diagnosed, can be treated definitively with iridectomy. Open-angle glaucoma is not a risk factor for angle closure glaucoma. Patients may wish to be examined to determine whether they are susceptible to angle closure, and have a prophylactic procedure (e.g., iridectomy), if they are susceptible.

5.10 Use in Patients with Concomitant Illness

Clinical experience with escitalopram in patients with certain concomitant systemic illnesses is limited. Caution is advisable in using escitalopram in patients with diseases or conditions that produce altered metabolism or hemodynamic responses.

Escitalopram has not been systematically evaluated in patients with a recent history of myocardial infarction or unstable heart disease. Patients with these diagnoses were generally excluded from clinical studies during escitalopram premarketing testing.

In subjects with hepatic impairment, clearance of racemic citalopram was decreased and plasma concentrations were increased. Escitalopram Capsules are not recommended in patients with hepatic impairment [see Use in Specific Populations (8.6)].

Because escitalopram is extensively metabolized, excretion of unchanged drug in urine is a minor route of elimination. Pharmacokinetics of escitalopram in patients with a creatinine clearance less than 20 mL/minute has not been evaluated, however, it should be used with caution in such patients [see Clinical Pharmacology (12.3)].

5.11 Sexual Dysfunction

Use of SSRIs, including Escitalopram Capsules, may cause symptoms of sexual dysfunction [see Adverse Reactions (6.1)]. In male patients, SSRI use may result in ejaculatory delay or failure, decreased libido, and erectile dysfunction. In female patients, SSRI use may result in decreased libido and delayed or absent orgasm.

It is important for prescribers to inquire about sexual function prior to initiation of Escitalopram Capsules and to inquire specifically about changes in sexual function during treatment, because sexual function may not be spontaneously reported. When evaluating changes in sexual function, obtaining a detailed history (including timing of symptom onset) is important because sexual symptoms may have other causes, including the underlying psychiatric disorder. Discuss potential management strategies to support patients in making informed decisions about treatment.

6 ADVERSE REACTIONS

The following adverse reactions are discussed in greater detail in other sections of the labeling:

- Suicidal Thoughts and Behaviors in Adolescents and Young Adults [see Warnings and Precautions (5.1)]
- Serotonin Syndrome [see Warnings and Precautions (5.2)]
- Discontinuation Syndrome [see Warnings and Precautions (5.3)]
- Seizures [see Warnings and Precautions (5.4)]
- Activation of Mania or Hypomania [see Warnings and Precautions (5.5)]
- Hyponatremia [see Warnings and Precautions (5.6)]
- Increased Risk of Bleeding [see Warnings and Precautions (5.7)]
- Interference with Cognitive and Motor Performance [see Warnings and Precautions (5.8)]
- Angle Closure Glaucoma [see Warnings and Precautions (5.9)]
- Use in Patients with Concomitant Illness [see Warnings and Precautions (5.10)]
- Sexual Dysfunction [see Warnings and Precautions (5.11)]

6.1 Clinical Trials Experience

Because clinical studies are conducted under widely varying conditions, adverse reaction rates observed in the clinical studies of a drug cannot be directly compared to rates in the clinical studies of another drug and may not reflect the rates observed in practice.

The safety of Escitalopram Capsules 15 mg once daily for the treatment of major depressive disorder (MDD) in adults younger than 65 years of age and pediatric patients 12 years of age and older and for the treatment of generalized anxiety disorder (GAD) in adults younger than 65 years of age is based upon adequate and well-controlled studies of another escitalopram product with dosing ranging from 10 to 20 mg once daily. The results of these adequate and well-controlled studies are presented below.

Clinical Trial Data Sources

Adults

Adverse reaction data in adults with MDD were collected from 715 patients who were exposed to escitalopram and from 592 patients who were exposed to placebo in double-blind, placebo-controlled trials. An additional 284 adults with MDD were newly exposed to escitalopram in open-label trials. The adverse reaction data in adults with GAD were collected from 429 patients exposed to escitalopram and from 427 patients exposed to placebo in double-blind, placebo-controlled trials.

Pediatric Patients

Adverse reaction data for pediatric patients with MDD were collected in double-blind placebo-controlled studies in 576 pediatric patients 6 to 17 years of age, (286 escitalopram, 290 placebo).

The safety and effectiveness of Escitalopram Capsules have not been established in pediatric patients less than 12 years of age with MDD.

Adverse Reactions Associated with Discontinuation of Treatment

Major Depressive Disorder in Adults

Among the 715 adults with MDD who received escitalopram in placebo-controlled trials, 6% discontinued treatment due to an adverse reaction, as compared to 2% of 592 patients receiving placebo. The rate of discontinuation for adverse reactions in patients assigned to a fixed dose of 20 mg/day escitalopram was 10%, which was significantly different from the rate of discontinuation for adverse reactions in patients receiving 10 mg/day escitalopram (4%) and placebo (3%). Adverse reactions that were associated with discontinuation in at least 1% of escitalopram-treated patients, and at least twice that of placebo, were nausea (2%) and ejaculation disorder (2% of male patients).

Major Depressive Disorder in Pediatric Patients

In pediatric patients 6 to 17 years of age with MDD, adverse reactions were associated with discontinuation in 3.5% of 286 patients receiving escitalopram and 1% of 290 patients receiving placebo. The most common adverse reaction (incidence at least 1% for escitalopram and greater than placebo) associated with discontinuation was insomnia (1% escitalopram, 0% placebo).

The safety and effectiveness of Escitalopram Capsules have not been established in pediatric patients less than 12 years of age with MDD.

Generalized Anxiety Disorder in Adults

Among the 429 adults with GAD who received escitalopram 10 to 20 mg/day in placebo-controlled trials, 8% discontinued treatment due to an adverse reaction, as compared to 4% of 427 patients receiving placebo. Adverse reactions that were associated with discontinuation in at least 1% of escitalopram-treated patients and at least twice the placebo rate were nausea (2%), insomnia (1%), and fatigue (1%).

Additional pediatric use information is approved for AbbVie Inc.’s LEXAPRO (escitalopram) tablets and LEXAPRO (escitalopram) oral solution. However, due to AbbVie Inc.’s marketing exclusivity rights, this drug product is not labeled with that information.

Incidence of Adverse Reactions in Placebo-Controlled Clinical Trials

Major Depressive Disorder in Adults

The most commonly observed adverse reactions in escitalopram-treated adults with MDD (incidence of approximately 5% or greater and approximately twice the placebo rate) were insomnia, ejaculation disorder (primarily ejaculatory delay), nausea, increased sweating, fatigue, and somnolence.

Table 2 enumerates the incidence, rounded to the nearest percent, of adverse reactions that occurred among 715 adults with MDD who received escitalopram at doses ranging from 10 to 20 mg/day in placebo-controlled trials. Reactions included are those occurring in 2% or more of escitalopram-treated patients and greater than the incidence in placebo-treated patients.

Table 2: Adverse Reactions (≥ 2% and greater than placebo) for Major Depressive Disorder in Adults in Placebo-Controlled Trials
Adverse Reaction | Escitalopram | Placebo
 | (N=715) % | (N=592) %
Autonomic Nervous System Disorders
Dry Mouth | 6 | 5
Sweating Increased | 5 | 2
Central & Peripheral Nervous System Disorders
Dizziness | 5 | 3
Gastrointestinal Disorders
Nausea | 15 | 7
Diarrhea | 8 | 5
Constipation | 3 | 1
Indigestion | 3 | 1
Abdominal Pain | 2 | 1
General
Influenza-like Symptoms | 5 | 4
Fatigue | 5 | 2
Psychiatric Disorders
Insomnia | 9 | 4
Somnolence | 6 | 2
Appetite Decreased | 3 | 1
Libido Decreased | 3 | 1
Respiratory System Disorders
Rhinitis | 5 | 4
Sinusitis | 3 | 2
Urogenital
Ejaculation Disorder^1,2 | 9 | <1
Impotence^2 | 3 | <1
Anorgasmia^3 | 2 | <1
^1Primarily ejaculatory delay.
^2Denominator used was for males only (N=225 escitalopram; N=188 placebo).
^3Denominator used was for females only (N=490 escitalopram; N=404 placebo).

Major Depressive Disorder in Pediatric Patients

The overall profile of adverse reactions in pediatric patients 6 to 17 years of age with MDD was generally similar to that seen in adult studies, as shown in Table 2. However, the following adverse reactions (excluding those which appear in Table 2 and those for which the coded terms were uninformative or misleading) were reported at an incidence of at least 2% for escitalopram and greater than placebo: back pain, urinary tract infection, vomiting, and nasal congestion.

The safety and effectiveness of Escitalopram Capsules have not been established in pediatric patients less than 12 years of age with MDD.

Generalized Anxiety Disorder in Adults

The most commonly observed adverse reactions in escitalopram-treated adults with GAD (incidence of approximately 5% or greater and approximately twice the placebo rate) were nausea, ejaculation disorder (primarily ejaculatory delay), insomnia, fatigue, decreased libido, and anorgasmia.

Table 3 enumerates the incidence, rounded to the nearest percent of adverse reactions that occurred among 429 escitalopram-treated adults with GAD who received 10 to 20 mg/day in placebo-controlled trials. Reactions included are those occurring in 2% or more of escitalopram-treated patients and for which the incidence was greater than the incidence in placebo-treated patients.

Table 3: Adverse Reactions (≥ 2% and greater than placebo) for Generalized Anxiety Disorder in Adults in Placebo-Controlled Trials
Adverse Reactions | Escitalopram | Placebo
 | (N=429) % | (N=427) %
Autonomic Nervous System Disorders
Dry Mouth | 9 | 5
Sweating Increased | 4 | 1
Central & Peripheral Nervous System Disorders
Headache | 24 | 17
Paresthesia | 2 | 1
Gastrointestinal Disorders
Nausea | 18 | 8
Diarrhea | 8 | 6
Constipation | 5 | 4
Indigestion | 3 | 2
Vomiting | 3 | 1
Abdominal Pain | 2 | 1
Flatulence | 2 | 1
Toothache | 2 | 0
General
Fatigue | 8 | 2
Influenza-like Symptoms | 5 | 4
Musculoskeletal System Disorder
Neck/Shoulder Pain | 3 | 1
Psychiatric Disorders
Somnolence | 13 | 7
Insomnia | 12 | 6
Libido Decreased | 7 | 2
Dreaming Abnormal | 3 | 2
Appetite Decreased | 3 | 1
Lethargy | 3 | 1
Respiratory System Disorders
Yawning | 2 | 1
Urogenital
Ejaculation Disorder^1,2 | 14 | 2
Anorgasmia^3 | 6 | <1
Menstrual Disorder | 2 | 1
^1Primarily ejaculatory delay.
^2Denominator used was for males only (N=182 escitalopram; N=195 placebo).
^3Denominator used was for females only (N=247 escitalopram; N=232 placebo).

Additional pediatric use information is approved for AbbVie Inc’s LEXAPRO (escitalopram) tablets and LEXAPRO (escitalopram) oral solution. However, due to AbbVie Inc’s marketing exclusivity rights, this drug product is not labeled with that information.

Dose Dependency of Adverse Reactions

The potential dose dependency of common adverse reactions (defined as an incidence rate of ≥5% in either the 10 mg or 20 mg escitalopram groups) was examined on the basis of the combined incidence of adverse reactions in two fixed-dose trials. The overall incidence rates of adverse reactions in 10 mg/day escitalopram-treated patients (66%) were similar to that of the placebo-treated patients (61%), while the incidence rate in 20 mg/day escitalopram-treated patients was greater (86%). Table 4 shows common adverse reactions that occurred in the 20 mg/day escitalopram group with an incidence that was approximately twice that of the 10 mg/day escitalopram group and approximately twice that of the placebo group.

Table 4: Dose Dependency of Common Adverse Reactions in Patients with Major Depressive Disorder*
Adverse Reaction | Placebo (N=311) | 10 mg/day Escitalopram** (N=310) | 20 mg/day Escitalopram** (N=125)
Insomnia | 4% | 7% | 14%
Diarrhea | 5% | 6% | 14%
Dry Mouth | 3% | 4% | 9%
Somnolence | 1% | 4% | 9%
Sweating Increased | <1% | 3% | 8%
Dizziness | 2% | 4% | 7%
Constipation | 1% | 3% | 6%
Fatigue | 2% | 2% | 6%
Indigestion | 1% | 2% | 6%
*Adverse reactions in the 20 mg/day escitalopram group occurred with an approximate incidence of twice the 10 mg/day escitalopram group and approximately twice that of placebo.
**Escitalopram Capsules are available only as a 15 mg dosage strength.

Male and Female Sexual Dysfunction with SSRIs

Although changes in sexual desire, sexual performance, and sexual satisfaction often occur as manifestations of a psychiatric disorder, they may also be a consequence of SSRI treatment. However, reliable estimates of the incidence and severity of untoward experiences involving sexual desire, performance, and satisfaction are difficult to obtain, in part because patients and healthcare providers may be reluctant to discuss them. Accordingly, estimates of the incidence of untoward sexual experience and performance cited in product labeling are likely to underestimate their actual incidence.

Table 5: Incidence of Sexual Adverse Reactions in Males or Females in Placebo-Controlled Clinical Trials
Adverse Reaction | Escitalopram | Placebo
 | Males Only
 | (N=407) % | (N=383) %
Ejaculation Disorder (primarily ejaculatory delay) | 12 | 1
Libido Decreased | 6 | 2
Impotence | 2 | <1
 | Females Only
 | (N=737) % | (N=636) %
Libido Decreased | 3 | 1
Anorgasmia | 3 | <1

There are no adequately designed studies examining sexual dysfunction with escitalopram treatment.

Priapism has been reported with all SSRIs.

Weight Changes

Patients treated with escitalopram in controlled trials did not differ from placebo-treated patients with regard to clinically important change in body weight.

ECG Changes

Electrocardiograms from another escitalopram product (N=625) and placebo (N=527) groups were compared with respect to outliers defined as subjects with QTc changes over 60 msec from baseline or absolute values over 500 msec post-dose, and subjects with heart rate increases to over 100 bpm or decreases to less than 50 bpm with a 25% change from baseline (tachycardic or bradycardic outliers, respectively). None of the patients in the escitalopram group had a QTcF interval >500 msec or a prolongation >60 msec compared to 0.2% of patients in the placebo group. The incidence of tachycardic outliers was 0.2% in the escitalopram and the placebo group. The incidence of bradycardic outliers was 0.5% in the escitalopram group and 0.2% in the placebo group.

Other Reactions Observed During the Premarketing Evaluation of Escitalopram Capsules

Other adverse reactions at an incidence of ≥1% and greater than placebo reported by the 1428 patients treated with another escitalopram product for periods of up to one year in double-blind or open-label clinical trials are shown below. The following list does not include adverse reactions 1) already listed in previous tables or elsewhere in the labeling, 2) for which a drug cause was remote, 3) which were so general as to be uninformative, 4) which were not considered to have clinically significant implications, or 5) which occurred at a rate equal to or less than placebo.

Cardiovascular: hypertension, palpitation.

Central and Peripheral Nervous System Disorders: light-headed feeling, migraine.

Gastrointestinal Disorders: abdominal cramp, heartburn, gastroenteritis.

General: allergy, chest pain, fever, hot flushes, pain in limb.

Metabolic and Nutritional Disorders: increased weight.

Musculoskeletal System Disorders: arthralgia, myalgia jaw stiffness.

Psychiatric Disorders: appetite increased, concentration impaired, irritability.

Reproductive Disorders/Female: menstrual cramps, menstrual disorder.

Respiratory System Disorders: bronchitis, coughing, nasal congestion, sinus congestion, sinus headache.

Skin and Appendages Disorders: rash.

Special Senses: vision blurred, tinnitus.

Urinary System Disorders: urinary frequency, urinary tract infection.

6.2 Post-Marketing Experience

The following adverse reactions have been identified during post-approval use of another escitalopram product. Because these reactions are reported voluntarily from a population of uncertain size, it is not always possible to reliably estimate their frequency or establish a causal relationship to drug exposure.

Blood and Lymphatic System Disorders: anemia, agranulocytis, aplastic anemia, hemolytic anemia, idiopathic thrombocytopenia purpura, leukopenia, thrombocytopenia.

Cardiac Disorders: atrial fibrillation, bradycardia, cardiac failure, myocardial infarction, tachycardia, torsade de pointes, ventricular arrhythmia, ventricular tachycardia.

Ear and Labyrinth Disorders: vertigo

Endocrine Disorders: diabetes mellitus, hyperprolactinemia, SIADH.

Eye Disorders: angle closure glaucoma, diplopia, mydriasis, visual disturbance.

Gastrointestinal Disorder: dysphagia, gastrointestinal hemorrhage, gastroesophageal reflux, pancreatitis, rectal hemorrhage.

General Disorders and Administration Site Conditions: abnormal gait, asthenia, edema, fall, feeling abnormal, malaise.

Hepatobiliary Disorders: fulminant hepatitis, hepatic failure, hepatic necrosis, hepatitis.

Immune System Disorders: allergic reaction, anaphylaxis.

Investigations: bilirubin increased, decreased weight, electrocardiogram QT prolongation, hepatic enzymes increased, hypercholesterolemia, INR increased, prothrombin decreased.

Metabolism and Nutrition Disorders: hyperglycemia, hypoglycemia, hypokalemia, hyponatremia.

Musculoskeletal and Connective Tissue Disorders: muscle cramp, muscle stiffness, muscle weakness, rhabdomyolysis.

Nervous System Disorders: akathisia, amnesia, ataxia, choreoathetosis, cerebrovascular accident, dysarthria, dyskinesia, dystonia, extrapyramidal disorders, grand mal seizures (or convulsions), hypoaesthesia, myoclonus, nystagmus, Parkinsonism, restless legs, seizures, syncope, tardive dyskinesia, tremor.

Pregnancy, Puerperium and Perinatal Conditions: spontaneous abortion.

Psychiatric Disorders: acute psychosis, aggression, agitation, anger, anxiety, apathy, completed suicide, confusion, depersonalization, depression aggravated, delirium, delusion, disorientation, feeling unreal, hallucinations (visual and auditory), mood swings, nervousness, nightmare, panic reaction, paranoia, restlessness, self-harm or thoughts of self-harm, suicide attempt, suicidal ideation, suicidal tendency.

Renal and Urinary Disorders: acute renal failure, dysuria, urinary retention.

Reproductive System and Breast Disorders: menorrhagia, priapism.

Respiratory, Thoracic and Mediastinal Disorders: anosmia, dyspnea, epistaxis, pulmonary embolism, hyposmia, pulmonary hypertension of the newborn.

Skin and Subcutaneous Tissue Disorders: alopecia, angioedema, dermatitis, drug reaction with eosinophilia and systemic symptoms (DRESS), ecchymosis, erythema multiforme, photosensitivity reaction, Stevens Johnson Syndrome, toxic epidermal necrolysis, urticaria.

Vascular Disorders: deep vein thrombosis, flushing, hypertensive crisis, hypotension, orthostatic hypotension, phlebitis, thrombosis.

7 DRUG INTERACTIONS

Table 6 presents clinically important drug interactions with Escitalopram Capsules.

Table 6: Clinically Important Drug Interactions with Escitalopram Capsules
Monoamine Oxidase Inhibitors (MAOIs)
Prevention or Management | Escitalopram Capsules are contraindicated in patients taking MAOIs, including MAOIs such as linezolid or intravenous methylene blue [see Dosage and Administration (2.6), Contraindications (4), Warnings and Precautions (5.2)].
Mechanism and Clinical Effect(s) | Concomitant use of SSRIs, including Escitalopram Capsules, and MAOIs increases the risk of serotonin syndrome.
Pimozide
Prevention or Management | Escitalopram Capsules are contraindicated in patients taking pimozide [see Contraindications (4)].
Mechanism and Clinical Effect(s) | Concomitant use of racemic citalopram with pimozide increases plasma concentrations of pimozide, a drug with a narrow therapeutic index, and may increase the risk of QT prolongation and/or ventricular arrhythmias compared to use of racemic citalopram alone. The mechanism of this pharmacodynamic interaction is not known [see Clinical Pharmacology (12.3)].
Other Serotonergic Drugs
Prevention or Management | Monitor patients for signs and symptoms of serotonin syndrome, particularly during escitalopram initiation and dosage increases. If serotonin syndrome occurs, consider discontinuation of Escitalopram Capsules and/or concomitant serotonergic drugs [see Warnings and Precautions (5.2)].
Mechanism and Clinical Effect(s) | Concomitant use of Escitalopram Capsules and other serotonergic drugs (including other SSRIs, SNRIs, triptans, tricyclic antidepressants, opioids, lithium, buspirone, amphetamines, tryptophan, and St. John's Wort) increases the risk of serotonin syndrome.
Drugs That Interfere With Hemostasis (NSAIDs, Aspirin, Warfarin, etc.)
Prevention or Management | Inform patients of the increased risk of bleeding associated with the concomitant use of Escitalopram Capsules and antiplatelet agents and anticoagulants. For patients taking warfarin, carefully monitor the international normalized ratio [see Warnings and Precautions (5.7)].
Mechanism and Clinical Effect(s) | Concomitant use of Escitalopram Capsules and an antiplatelet or anticoagulant may potentiate the risk of bleeding.
Sumatriptan
Prevention or Management | If concomitant use of Escitalopram Capsules and sumatriptan is clinically warranted, appropriate observation of the patient is advised [see Warnings and Precautions (5.2)].
Mechanism and Clinical Effect(s) | There have been postmarketing reports of weakness, hyperreflexia, and incoordination following the concomitant use of an SSRI and sumatriptan.
Lithium
Prevention or Management | Monitor plasma lithium levels with appropriate adjustment to the lithium dose in accordance with standard clinical practice.
Mechanism and Clinical Effect(s) | Because lithium may enhance the serotonergic effects of escitalopram, caution should be exercised when Escitalopram Capsules is used concomitantly with lithium.
Alcohol
Prevention or Management | Concomitant use of Escitalopram Capsules and alcohol is not recommended.
Mechanism and Clinical Effect(s) | Alcohol may potentiate the psychotropic effects of escitalopram.
Drugs Metabolized by CYP2D6
Prevention or Management | The clinical significance of this finding is unknown. Exercise caution during coadministration of Escitalopram Capsules and drugs metabolized by CYP2D6.
Mechanism and Clinical Effect(s) | Coadministration of escitalopram with the tricyclic antidepressant desipramine, a substrate for CYP2D6, resulted in a 40% increase in Cmax and a 100% increase in AUC of desipramine.

8 USE IN SPECIFIC POPULATIONS

8.1 Pregnancy

Pregnancy Exposure Registry

There is a pregnancy exposure registry that monitors pregnancy outcomes in women exposed to antidepressants during pregnancy. Healthcare providers are encouraged to advise patients to register by calling the National Pregnancy Registry for Antidepressants at 1-844-405-6185 or visiting online at https://womensmentalhealth.org/research/pregnancyregistry/antidepressants.

Risk Summary

Based on data from published observational studies, exposure to SSRIs, particularly in the month before delivery, has been associated with a less than 2-fold increase in the risk of postpartum hemorrhage [see Warnings and Precautions (5.7), Clinical Considerations].

Available data from published epidemiologic studies and postmarketing reports have not established an increased risk of major birth defects or miscarriage. There are risks of persistent pulmonary hypertension of the newborn (PPHN) (see Data) and poor neonatal adaptation (see Clinical Considerations) with exposure to selective serotonin reuptake inhibitors (SSRIs), including Escitalopram Capsules, during pregnancy. There are risks associated with untreated depression in pregnancy (see Clinical Considerations).

In animal reproduction studies, both escitalopram and racemic citalopram have been shown to have adverse effects on embryo/fetal and postnatal development, including fetal structural abnormalities, when administered at doses greater than human therapeutic doses (see Data).

The estimated background risk of major birth defects and miscarriage for the indicated population is unknown. All pregnancies have a background risk of birth defect, loss, or other adverse outcomes. In the U.S. general population, the estimated background risk of major birth defects and miscarriage in the clinically recognized pregnancies is 2 to 4% and 15 to 20%, respectively.

Clinical Considerations

Disease-associated maternal risk and/or embryo/fetal risk

Women who discontinue antidepressants are more likely to experience a relapse of major depression than women who continue antidepressants. This finding is from a prospective longitudinal study of 201 pregnant women with a history of major depression, who were euthymic and taking antidepressants at the beginning of pregnancy. Consider the risk of untreated depression when discontinuing or changing treatment with antidepressant medication during pregnancy and postpartum.

Maternal Adverse Reactions

Use of Escitalopram Capsules in the month before delivery may be associated with an increased risk of postpartum hemorrhage [see Warnings and Precautions (5.7)].

Fetal/Neonatal adverse reactions

Neonates exposed to SSRIs or SNRIs, including Escitalopram Capsules, late in third trimester have developed complications requiring prolonged hospitalization, respiratory support, and tube feeding. Such complications can arise immediately upon delivery. Reported clinical findings have included respiratory distress, cyanosis, apnea, seizures, temperature instability, feeding difficulty, vomiting, hypoglycemia, hypotonia, hypertonia, hyperreflexia, tremor, jitteriness, irritability, and constant crying. These features are consistent with either a direct toxic effect of SSRIs and SNRIs or, possibly, a drug discontinuation syndrome. It should be noted that, in some cases, the clinical picture is consistent with serotonin syndrome [see Warnings and Precautions (5.2)].

Data

Human Data

Exposure to SSRIs, particularly later in pregnancy, may increase the risk for PPHN. PPHN occurs in 1-2 per 1000 live births in the general populations and is associated with substantial neonatal morbidity and mortality.

Animal Data

In a rat embryo/fetal development study, oral administration of escitalopram (56, 112, or 150 mg/kg/day) to pregnant animals during the period of organogenesis resulted in decreased fetal body weight and associated delays in ossification at the two higher doses [approximately ≥ 55 times the maximum recommended human dose (MRHD) of 20 mg/day on a mg/m^2 basis]. Maternal toxicity (clinical signs and decreased body weight gain and food consumption), mild at 56 mg/kg/day, was present at all dose levels. The developmental no-effect dose of 56 mg/kg/day is approximately 27 times the MRHD of 20 mg on a mg/m^2 basis. No malformations were observed at any of the doses tested (as high as 73 times the MRHD on a mg/m^2 basis).

When female rats were treated with escitalopram (6, 12, 24, or 48 mg/kg/day) during pregnancy and through weaning, slightly increased offspring mortality and growth retardation were noted at 48 mg/kg/day which is approximately 23 times the MRHD of 20 mg on a mg/m^2 basis. Slight maternal toxicity (clinical signs and decreased body weight gain and food consumption) was seen at this dose. Slightly increased offspring mortality was also seen at 24 mg/kg/day. The no-effect dose was 12 mg/kg/day which is approximately 6 times the MRHD of 20 mg on a mg/m^2 basis.

In two rat embryo/fetal development studies, oral administration of racemic citalopram (32, 56, or 112 mg/kg/day) to pregnant animals during the period of organogenesis resulted in decreased embryo/fetal growth and survival and an increased incidence of fetal abnormalities (including cardiovascular and skeletal defects) at the high dose, which is approximately 18 times the MRHD of 60 mg/day on a mg/m^2 basis. This dose was also associated with maternal toxicity (clinical signs, decreased body weight gain). The developmental no-effect dose was 56 mg/kg/day is approximately 9 times the MRHD on a mg/m^2 basis. In a rabbit study, no adverse effects on embryo/fetal development were observed at doses of racemic citalopram of up to 16 mg/kg/day, or approximately 5 times the MRHD on a mg/m^2 basis. Thus, developmental effects of racemic citalopram were observed at a maternally toxic dose in the rat and were not observed in the rabbit.

When female rats were treated with racemic citalopram (4.8, 12.8, or 32 mg/kg/day) from late gestation through weaning, increased offspring mortality during the first 4 days after birth and persistent offspring growth retardation were observed at the highest dose, which is approximately 5 times the MRHD of 60 mg on a mg/m^2 basis. The no-effect dose was 12.8 mg/kg/day is approximately 2 times the MRHD on a mg/m^2 basis. Similar effects on offspring mortality and growth were seen when dams were treated throughout gestation and early lactation at doses ≥ 24 mg/kg/day, approximately 4 times the MRHD on a mg/m^2 basis. A no-effect dose was not determined in that study.

8.2 Lactation

Risk Summary

Data from the published literature report the presence of escitalopram and desmethylescitalopram in human milk (see Data). There are reports of excessive sedation, restlessness, agitation, poor feeding and poor weight gain in infants exposed to escitalopram, through breast milk (see Clinical Considerations). There are no data on the effects of escitalopram or its metabolites on milk production. The developmental and health benefits of breastfeeding should be considered along with the mother’s clinical need for Escitalopram Capsules and any potential adverse effects on the breastfed child from Escitalopram Capsules or from the underlying maternal condition.

Clinical Considerations

Infants exposed to Escitalopram Capsules should be monitored for excess sedation, restlessness, agitation, poor feeding and poor weight gain.

Data

A study of 8 nursing mothers on another escitalopram product with daily doses of 10-20 mg/day showed that exclusively breast-fed infants receive approximately 3.9% of the maternal weight-adjusted dose of escitalopram and 1.7% of the maternal weight-adjusted dose of desmethylcitalopram.

8.4 Pediatric Use

Major Depressive Disorder

The safety and effectiveness of Escitalopram Capsules for the treatment of major depressive disorder (MDD) have been established in pediatric patients 12 years of age and older. Use of Escitalopram Capsules for this indication is supported by evidence from adequate and well-controlled studies of another escitalopram product in adults with additional evidence from an 8-week, flexible-dose, placebo-controlled study that compared escitalopram 10 mg to 20 mg once daily to placebo in pediatric patients 12 to 17 years of age with MDD [see Clinical Studies (14.1)]. The safety of escitalopram was similar to adult patients with MDD [see Adverse Reactions (6.1)].

The safety and effectiveness of Escitalopram Capsules for the treatment of MDD have not been established in pediatric patients younger than 12 years of age. In a 24-week, open-label safety study in 118 pediatric patients aged 7 to 11 years who had MDD, the safety findings were consistent with the known safety and tolerability profile for escitalopram.

Antidepressants increase the risk of suicidal thoughts and behaviors in pediatric patients [see Warnings and Precautions (5.1)]. Decreased appetite and weight loss have been observed in association with the use of SSRIs. Consequently, regular monitoring of weight and growth should be performed in children and adolescents treated with an SSRI such as escitalopram.

Generalized Anxiety Disorder

The safety and effectiveness of escitalopram for the treatment of generalized anxiety disorder have not been established in pediatric patients younger than 7 years of age.

Additional pediatric use information is approved for AbbVie Inc.’s LEXAPRO (escitalopram) tablets and LEXAPRO (escitalopram) oral solution. However, due to AbbVie Inc.’s marketing exclusivity rights, this drug product is not labeled with that information.

Juvenile Animal Toxicity Data

In a juvenile animal study, male and female rats were administered escitalopram at 5, 40, or 80 mg/kg/day by oral gavage from postnatal day (PND) 21 to PND 69. A delay in sexual maturation was observed in both males and females at ≥ 40 mg/kg/day with a No Observed Adverse Effect Level (NOAEL) of 5 mg/kg/day. This NOAEL was associated with plasma AUC levels less than those measured at the maximum recommended human dose (MRHD) in pediatrics (20 mg). However, there was no effect on reproductive function. Increased motor activity (both ambulatory and fine movements) was observed in females prior to daily dosing at ≥ 40 mg/kg/day (3.5 times the MRHD based on AUC levels). A reversible disruption of learning and memory function was observed in males at 80 mg/kg/day with a NOAEL of 40 mg/kg/day, which was associated with an AUC level 3.5 times those measured at the MRHD in pediatrics. There was no effect on learning and memory function in treated female rats.

8.5 Geriatric Use

Escitalopram Capsules are not indicated in geriatric patients. Avoid use of Escitalopram Capsules in geriatric patients because the recommended dosage in these patients can not be achieved with the available dosage strength.

Approximately 69 patients (6%) of the 1,144 patients receiving escitalopram in controlled trials of another escitalopram product in major depressive disorder and GAD were 60 years of age or older [see Clinical Studies (14.1, 14.2)].

In two pharmacokinetic studies, escitalopram half-life was increased by approximately 50% in subjects 65 years and older as compared to young subjects and Cmax was unchanged [see Clinical Pharmacology (12.3)].

SSRIs, including escitalopram, have been associated with cases of clinically significant hyponatremia in geriatric patients, who may be at greater risk for this adverse reaction [see Warnings and Precautions (5.6)].

Of 4,422 patients in clinical studies of racemic citalopram, 1,357 were 60 and over, 1,034 were 65 and over, and 457 were 75 and over.

8.6 Hepatic Impairment

Escitalopram Capsules are not recommended in patients with hepatic impairment because the recommended dosage in such patients cannot be achieved with the available dosage strength of Escitalopram Capsules.

Increased citalopram exposure occurs in patients with hepatic impairment [see Clinical Pharmacology (12.3)].

9 DRUG ABUSE AND DEPENDENCE

9.1 Controlled Substance

Escitalopram Capsules contain the active ingredient escitalopram, which is not a controlled substance.

9.2 Abuse

Animal studies suggest that the abuse liability of racemic citalopram is low. Escitalopram has not been systematically studied in humans for its potential for abuse. The premarketing clinical experience with escitalopram did not reveal any drug-seeking behavior. However, these observations were not systematic and it is not possible to predict on the basis of this limited experience the extent to which a CNS-active drug will be misused, and/or abused once marketed. Consequently, healthcare providers should carefully evaluate Escitalopram Capsules patients for history of drug abuse and follow such patients closely, observing them for signs of misuse or abuse (e.g., incrementations of dosage, drug-seeking behavior).

9.3 Dependence

Escitalopram has not been systematically studied in humans for its potential for tolerance or physical dependence.

10 OVERDOSAGE

The following have been reported with escitalopram overdosage:

- Seizures, which may be delayed, and altered mental status including coma.
- Cardiovascular toxicity, which may be delayed, including QRS and QTc interval prolongation, wide complex tachyarrhythmias, and torsade de pointes. Hypertension most commonly seen, but rarely can see hypotension alone or with co-ingestants including alcohol.
- Serotonin syndrome (patients with a multiple drug overdosage with other proserotonergic drugs may have a higher risk).

Prolonged cardiac monitoring is recommended in Escitalopram Capsules overdosage due to the arrhythmia risk.

Gastrointestinal decontamination with activated charcoal should be considered in patients who present early after an Escitalopram Capsules overdose.

As with the management of all overdosage, the possibility of multiple drug ingestion should be considered. Consider contacting the Poison Help line (1-800-222-1222) or a medical toxicologist for additional overdose management recommendations.

11 DESCRIPTION

Escitalopram Capsules contain escitalopram, a selective serotonin reuptake inhibitor (SSRI), present as escitalopram oxalate salt. Escitalopram is the pure S- enantiomer (single isomer) of the racemic bicyclic phthalane derivative citalopram. Escitalopram oxalate is designated S-(+)-1-[3(dimethyl-amino)propyl]-1-(p-fluorophenyl)-5-phthalancarbonitrile oxalate with the following structural formula:

The molecular formula is C20H21FN2O • C2H2O4 and the molecular weight is 414.43. Escitalopram oxalate occurs as a fine, white to slightly yellow powder and is freely soluble in methanol and in dimethyl sulphoxide, sparingly soluble in water and in alcohol, very slightly soluble in ethyl acetate and in isopropyl alcohol, and insoluble in heptane.

Escitalopram Capsules are intended for oral administration and are available only in a 15 mg strength. The capsules contain 15 mg escitalopram (equivalent to 19.16 mg escitalopram oxalate) and the following inactive ingredients: croscarmellose sodium, copovidone, FD&C Blue #1, FD&C Red #40, gelatin, magnesium stearate, microcrystalline cellulose, sodium lauryl sulfate, talc, and titanium dioxide.

12 CLINICAL PHARMACOLOGY

12.1 Mechanism of Action

The mechanism of antidepressant action of escitalopram, the S-enantiomer of racemic citalopram, is presumed to be linked to potentiation of serotonergic activity in the central nervous system (CNS) resulting from its inhibition of CNS neuronal reuptake of serotonin (5-HT).

12.2 Pharmacodynamics

In vitro and in vivo studies in animals suggest that escitalopram is a highly selective serotonin reuptake inhibitor (SSRI) with minimal effects on norepinephrine and dopamine neuronal reuptake. Escitalopram is at least 100-fold more potent than the R-enantiomer with respect to inhibition of 5-HT reuptake and inhibition of 5-HT neuronal firing rate. Tolerance to a model of antidepressant effect in rats was not induced by long-term (up to 5 weeks) treatment with escitalopram. Escitalopram has no or very low affinity for serotonergic (5-HT1-7) or other receptors including alpha- and beta-adrenergic, dopamine (D1-5), histamine (H1-3), muscarinic (M1-5), and benzodiazepine receptors. Escitalopram also does not bind to, or has low affinity for, various ion channels including Na^+, K^+, Cl^-, and Ca^++ channels. Antagonism of muscarinic, histaminergic, and adrenergic receptors has been hypothesized to be associated with various anticholinergic, sedative, and cardiovascular side effects of other psychotropic drugs.

In vitro studies show that escitalopram is at least 7 and 27 times more potent than S-demethylcitalopram (S-DCT) and S-didemethylcitalopram (S-DDCT), respectively, in the inhibition of serotonin reuptake, suggesting that the metabolites of escitalopram do not contribute significantly to the antidepressant actions of escitalopram. S-DCT and S-DDCT also have no or very low affinity for serotonergic (5-HT1-7) or other receptors including alpha- and beta-adrenergic, dopamine (D1-5), histamine (H1-3), muscarinic (M1-5), and benzodiazepine receptors. S-DCT and S-DDCT also do not bind to various ion channels including Na^+, K^+, Cl^-, and Ca^++ channels.

Alcohol

Escitalopram did not potentiate the cognitive and motor effects of alcohol in a clinical trial [see Drug Interactions (7)].

Cardiac Electrophysiology

QTcF interval was evaluated in a randomized, placebo and active (moxifloxacin 400 mg) controlled cross-over, escalating multiple dose study in 113 healthy subjects. The maximum mean (95% upper confidence bound) difference from the placebo arm were 4.5 (6.4) and 10.7 (12.7) msec for 10 mg and 30 mg (1.5 times the maximum recommend dose) escitalopram given once daily, respectively. Based on the established exposure-response relationship, the predicted QTcF change from placebo arm (95% confidence interval) under the Cmax for the dose of 20 mg is 6.6 (7.9) msec. Escitalopram 30 mg given once daily resulted in mean Cmax of 1.7-fold higher than the mean Cmax for the maximum recommended dose of another escitalopram product at steady state (20 mg). The exposure under the 30 mg dose is similar to the steady state concentrations expected in CYP2C19 poor metabolizers following a dose of 20 mg.

12.3 Pharmacokinetics

The single- and multiple-dose pharmacokinetics of escitalopram are linear and dose-proportional in a dose range of 10 to 30 mg/day.

With once-daily dosing, steady state plasma concentrations are achieved within approximately one week. At steady state, the extent of accumulation of escitalopram in plasma in young healthy subjects was 2.2-2.5 times the plasma concentrations observed after a single dose.

Absorption

The absolute bioavailability of citalopram is about 80% relative to an intravenous dose.

Effect of Food

Following the administration of a single oral dose of 15 mg Escitalopram Capsules to healthy volunteers, peak blood plasma levels occur at about (Tmax median) 4.5 hours under fasting condition and 5.0 hours under fed condition. Absorption of escitalopram is not affected by food.

Distribution

The binding of escitalopram to human plasma proteins is approximately 56%. The volume of distribution of citalopram is about 12 L/kg. Data specific on escitalopram are unavailable.

Elimination

Biotransformation of escitalopram is mainly hepatic, with a mean terminal half-life of about 27-32 hours. The oral clearance of escitalopram is 600 mL/min, with approximately 7% of that due to renal clearance.

Metabolism

Escitalopram is metabolized to S-demethylcitalopram (S-DCT) and S-didemethylcitalopram (S-DDCT). In humans, unchanged escitalopram is the predominant compound in plasma. At steady state, the concentration of the escitalopram metabolite S-DCT in plasma is approximately one-third that of escitalopram. The level of S-DDCT was not detectable in most subjects. In vitro studies using human liver microsomes indicated that CYP3A4 and CYP2C19 are the primary isozymes involved in the N-demethylation of escitalopram.

Excretion

Following oral administrations of escitalopram, the fraction of drug recovered in the urine as escitalopram and S-DCT is about 8% and 10%, respectively.

Specific Populations

Pediatric Patients

Pediatric patients 12 to 17 years of age: In a single dose study of 10 mg escitalopram, AUC of escitalopram decreased by 19%, and Cmax increased by 26% in healthy pediatric subjects 12 to 17 years of age compared to adults. Following multiple dosing of 40 mg/day citalopram, escitalopram elimination half-life, steady-state Cmax and AUC were similar in pediatric patients 12 to 17 years of age with MDD compared to adults [see Use in Specific Populations (8.4)].

Additional pediatric use information is approved for AbbVie Inc.’s LEXAPRO (escitalopram) tablets and LEXAPRO (escitalopram) oral solution. However, due to AbbVie Inc.’s marketing exclusivity rights, this drug product is not labeled with that information.

Geriatric Patients

Escitalopram pharmacokinetics in subjects ≥ 65 years of age were compared to adults in a single-dose and a multiple-dose study. Escitalopram AUC and half-life were increased by approximately 50% in geriatric subjects, and Cmax was unchanged [see Use in Specific Populations (8.5)].

Male and Female Patients

Based on data from single- and multiple-dose studies measuring escitalopram in geriatric, young adults, and adolescents, no dosage adjustment on the basis of gender is needed.

Patients with Hepatic Impairment

Citalopram oral clearance was reduced by 37% and half-life was doubled in patients with reduced hepatic function compared to normal subjects [see Use in Specific Populations (8.6)].

Patients with Renal Impairment

In patients with mild to moderate renal function impairment, oral clearance of citalopram was reduced by 17% compared to normal subjects. No information is available about the pharmacokinetics of escitalopram in patients with severely reduced renal function (creatinine clearance < 20 mL/min).

Drug Interaction Studies

In vitro enzyme inhibition data did not reveal an inhibitory effect of escitalopram on CYP3A4, -1A2, -2C9, -2C19, and -2E1. Based on in vitro data, escitalopram would be expected to have little inhibitory effect on in vivo metabolism mediated by these cytochromes. While in vivo data to address this question are limited, results from drug interaction studies suggest that escitalopram, at a dose of 20 mg, has no 3A4 inhibitory effect and a modest 2D6 inhibitory effect [see Drug Interactions (7)].

CYP3A4 and CYP2C19 Inhibitors

In vitro studies indicated that CYP3A4 and -2C19 are the primary enzymes involved in the metabolism of escitalopram. However, coadministration of escitalopram (20 mg) and ritonavir (600 mg), a potent inhibitor of CYP3A4, did not significantly affect the pharmacokinetics of escitalopram. Because escitalopram is metabolized by multiple enzyme systems, inhibition of a single enzyme may not appreciably decrease escitalopram clearance.

Carbamazepine

Combined administration of racemic citalopram (40 mg/day for 14 days) and carbamazepine (titrated to 400 mg/day for 35 days) did not significantly affect the pharmacokinetics of carbamazepine, a CYP3A4 substrate. Although trough citalopram plasma levels were unaffected, given the enzyme-inducing properties of carbamazepine, the possibility that carbamazepine might increase the clearance of escitalopram should be considered if the two drugs are co-administered.

Cimetidine

In subjects who had received 21 days of 40 mg/day racemic citalopram, combined administration of 400 mg twice a day cimetidine for 8 days resulted in an increase in citalopram AUC and Cmax of 43% and 39%, respectively. The clinical significance of these findings is unknown.

Digoxin

In subjects who had received 21 days of 40 mg/day racemic citalopram, combined administration of citalopram and digoxin (single dose of 1 mg) did not significantly affect the pharmacokinetics of either citalopram or digoxin.

Lithium

Coadministration of racemic citalopram (40 mg/day for 10 days) and lithium (30 mmol/day for 5 days) had no significant effect on the pharmacokinetics of citalopram or lithium.

Theophylline

Combined administration of racemic citalopram (40 mg/day for 21 days) and the CYP1A2 substrate theophylline (single dose of 300 mg) did not affect the pharmacokinetics of theophylline. The effect of theophylline on the pharmacokinetics of citalopram was not evaluated.

Ketoconazole

Combined administration of racemic citalopram (40 mg) and ketoconazole (200 mg), a potent CYP3A4 inhibitor, decreased the Cmax and AUC of ketoconazole by 21% and 10%, respectively, and did not significantly affect the pharmacokinetics of citalopram.

Ritonavir

Combined administration of a single dose of ritonavir (600 mg), both a CYP3A4 substrate and a potent inhibitor of CYP3A4, and escitalopram (20 mg) did not affect the pharmacokinetics of either ritonavir or escitalopram.

Triazolam

Combined administration of racemic citalopram (titrated to 40 mg/day for 28 days) and the CYP3A4 substrate triazolam (single dose of 0.25 mg) did not significantly affect the pharmacokinetics of either citalopram or triazolam.

Metoprolol

Administration of 20 mg/day escitalopram for 21 days in healthy volunteers resulted in a 50% increase in Cmax and 82% increase in AUC of the beta-adrenergic blocker metoprolol (given in a single dose of 100 mg). Increased metoprolol plasma levels have been associated with decreased cardioselectivity. Coadministration of escitalopram and metoprolol had no clinically significant effects on blood pressure or heart rate.

Warfarin

Administration of 40 mg/day racemic citalopram for 21 days did not affect the pharmacokinetics of warfarin, a CYP3A4 substrate. Prothrombin time was increased by 5%. The clinical significance of these findings is unknown.

13 NONCLINICAL TOXICOLOGY

13.1 Carcinogenesis, Mutagenesis, Impairment of Fertility

Carcinogenesis

Racemic citalopram was administered in the diet to NMRI/BOM strain mice and COBS WI strain rats for 18 and 24 months, respectively. There was no evidence for carcinogenicity of racemic citalopram in mice receiving up to 240 mg/kg/day. There was an increased incidence of small intestine carcinoma in rats receiving 8 or 24 mg/kg/day racemic citalopram. A no-effect dose for this finding was not established. The relevance of these findings to humans is unknown.

Mutagenesis

Racemic citalopram was mutagenic in the in vitro bacterial reverse mutation assay (Ames test) in 2 of 5 bacterial strains (Salmonella TA98 and TA1537) in the absence of metabolic activation. It was clastogenic in the in vitro Chinese hamster lung cell assay for chromosomal aberrations in the presence and absence of metabolic activation. Racemic citalopram was not mutagenic in the in vitro mammalian forward gene mutation assay (HPRT) in mouse lymphoma cells or in a coupled in vitro/in vivo unscheduled DNA synthesis (UDS) assay in rat liver. It was not clastogenic in the in vitro chromosomal aberration assay in human lymphocytes or in two in vivo mouse micronucleus assays.

Impairment of Fertility

When racemic citalopram was administered orally to 16 male and 24 female rats prior to and throughout mating and gestation at doses of 32, 48, and 72 mg/kg/day, mating was decreased at all doses, and fertility was decreased at doses ≥ 32 mg/kg/day. Gestation duration was increased at 48 mg/kg/day.

13.2 Animal Toxicology and/or Pharmacology

Retinal Changes in Rats

Pathologic changes (degeneration/atrophy) were observed in the retinas of albino rats in the 2-year carcinogenicity study with racemic citalopram. There was an increase in both incidence and severity of retinal pathology in both male and female rats receiving 80 mg/kg/day. Similar findings were not present in rats receiving 24 mg/kg/day of racemic citalopram for two years, in mice receiving up to 240 mg/kg/day of racemic citalopram for 18 months, or in dogs receiving up to 20 mg/kg/day of racemic citalopram for one year.

Additional studies to investigate the mechanism for this pathology have not been performed, and the potential significance of this effect in humans has not been established.

Cardiovascular Changes in Dogs

In a one-year toxicology study, 5 of 10 beagle dogs receiving oral racemic citalopram doses of 8 mg/kg/day died suddenly between weeks 17 and 31 following initiation of treatment. Sudden deaths were not observed in rats at doses of racemic citalopram up to 120 mg/kg/day, which produced plasma levels of citalopram and its metabolites demethylcitalopram and didemethylcitalopram (DDCT) similar to those observed in dogs at 8 mg/kg/day. A subsequent intravenous dosing study demonstrated that in beagle dogs, racemic DDCT caused QT prolongation, a known risk factor for the observed outcome in dogs.

14 CLINICAL STUDIES

14.1 Major Depressive Disorder

The efficacy of Escitalopram Capsules 15 mg once daily for the treatment for major depressive disorder (MDD) in adults younger than 65 years of age and pediatric patients 12 years of age and older is based upon adequate and well-controlled studies of another escitalopram product with dosing ranging from 10 to 20 mg once daily. The results of these adequate and well-controlled studies are presented below.

Adults

The efficacy of escitalopram for the treatment of MDD in adults was established in three, 8-week, placebo-controlled studies conducted in outpatients between 18 and 65 years of age who met DSM-IV criteria for MDD. The primary outcome in all three studies was change from baseline to endpoint in the Montgomery Asberg Depression Rating Scale (MADRS).

A fixed-dose study compared 10 mg daily escitalopram and 20 mg daily escitalopram to placebo and 40 mg daily citalopram. The 10 mg daily and 20 mg daily escitalopram treatment groups showed statistically significant greater mean improvement compared to placebo on the MADRS. The 10 mg and 20 mg escitalopram groups were similar on this outcome measure.

In a second fixed-dose study of 10 mg daily escitalopram and placebo, the 10 mg daily escitalopram treatment group showed statistically significant greater mean improvement compared to placebo on the MADRS.

In a flexible-dose study, comparing escitalopram, titrated between 10 mg and 20 mg daily, to placebo and citalopram, titrated between 20 mg and 40 mg daily, the escitalopram treatment group showed statistically significant greater mean improvement compared to placebo on the MADRS.

Analyses of the relationship between treatment outcome and age, gender, and race did not suggest any differential responsiveness on the basis of these patient characteristics.

In a longer-term trial, 274 patients meeting (DSM-IV) criteria for MDD, who had responded during an initial 8 week, open-label treatment phase with escitalopram 10 mg or 20 mg daily, were randomized to continuation of escitalopram at their same dose, or to placebo, for up to 36 weeks of observation for relapse. Response during the open-label phase was defined by having a decrease of the MADRS total score to ≤ 12. Relapse during the double-blind phase was defined as an increase of the MADRS total score to ≥ 22, or discontinuation due to insufficient clinical response. Patients receiving continued escitalopram experienced a statistically significant longer time to relapse compared to those receiving placebo.

Pediatric Patients 12 Years of Age and Older

The efficacy of escitalopram for the treatment of MDD in pediatric patients 12 to 17 years of age was established in an 8-week, flexible-dose, placebo-controlled study that compared escitalopram (10 mg to 20 mg daily) to placebo in outpatients 12 to 17 years of age inclusive who met DSM-IV criteria for MDD. The primary outcome was change from baseline to endpoint in the Children’s Depression Rating Scale - Revised (CDRS-R). In this study, escitalopram showed statistically significant greater mean improvement compared to placebo on the CDRS-R.

The efficacy of escitalopram for the treatment of MDDin pediatric patients 12 to 17 years of age was established, in part, on the basis of extrapolation from the 8-week, flexible-dose, placebo-controlled study with racemic citalopram 20 mg to 40 mg daily. In this outpatient study in pediatric patients 7 to 17 years of age who met DSM-IV criteria for MDD, citalopram treatment showed statistically significant greater mean improvement from baseline, compared to placebo, on the CDRS-R; the positive results for this trial largely came from the 12 to 17 year subgroup.

Two additional flexible-dose, placebo-controlled MDD studies (one escitalopram study in patients ages 7 to 17 years and one citalopram study in patients ages 13 to 18 years) did not demonstrate efficacy. The safety and effectiveness of Escitalopram Capsules have not been established in pediatric patients less than 12 years of age with MDD.

14.2 Generalized Anxiety Disorder

The efficacy of Escitalopram Capsules 15 mg once daily for the treatment for generalized anxiety disorder (GAD) in adults younger than 65 years of age is based upon adequate and well-controlled studies of another escitalopram product with dosing ranging from 10 to 20 mg once daily. The results of these adequate and well-controlled studies are presented below.

The efficacy of escitalopram for the treatment of GAD in adults was demonstrated in three, 8-week, multicenter, flexible-dose, placebo-controlled studies that compared escitalopram (10 mg to 20 mg daily) to placebo in outpatients between 18 and 80 years of age who met DSM-IV criteria for GAD. In all three studies, escitalopram showed statistically significant greater mean improvement compared to placebo on the Hamilton Anxiety Scale (HAM-A).

There were too few patients in differing ethnic and age groups to adequately assess whether or not escitalopram has differential effects in these groups. There was no difference in response to escitalopram between men and women.

Additional pediatric use information is approved for AbbVie Inc.’s LEXAPRO (escitalopram) tablets and LEXAPRO (escitalopram) oral solution. However, due to AbbVie Inc.’s marketing exclusivity rights, this drug product is not labeled with that information.

16 HOW SUPPLIED/STORAGE AND HANDLING

How Supplied

15 mg capsules:

Hard shell gelatin capsules, with “ALM” printed axially on the light blue opaque cap and “795” printed axially on the blue opaque body. All printing is in black ink.

NDC 52427-795-30, Bottle of 30 capsules with a child-resistant closure

Storage and Handling

Store at 20°C to 25°C (68°F to 77°F); excursions permitted to 15°C to 30°C (59°F to 86°F) [see USP Controlled Room Temperature].

17 PATIENT COUNSELING INFORMATION

Advise the patient to read the FDA-approved patient labeling (Medication Guide).

Suicidal Thoughts and Behaviors

Advise patients and caregivers to look for the emergence of suicidal ideation and behavior, especially early during treatment and when the dosage is adjusted up or down, and instruct them to report such symptoms to their healthcare provider [see Boxed Warning, Warnings and Precautions (5.1)].

Serotonin Syndrome

Caution patients about the risk of serotonin syndrome, particularly with the concomitant use of Escitalopram Capsules with other serotonergic drugs including triptans, tricyclic antidepressants, opioids, lithium, tryptophan, buspirone, amphetamines, St. John’s Wort, and with drugs that impair metabolism of serotonin (in particular, MAOIs, both those intended to treat psychiatric disorders and also others, such as linezolid). Instruct patients to contact their health care provider or report to the emergency room if they experience signs or symptoms of serotonin syndrome [see Warnings and Precautions (5.2), Drug Interactions (7)].

Discontinuation Syndrome

Advise patients not to abruptly discontinue Escitalopram Capsules and to discuss any tapering regimen with their healthcare provider. Inform patients that adverse reactions can occur when Escitalopram Capsules are discontinued [see Warnings and Precautions (5.3)].

Activation of Mania or Hypomania

Advise patients and their caregivers to observe for signs of activation of mania/hypomania and instruct them to report such symptoms to the healthcare provider [see Warnings and Precautions (5.5)].

Increased Risk of Bleeding

Inform patients about the concomitant use of Escitalopram Capsules with NSAIDs, aspirin, warfarin, other antiplatelet drugs, or other anticoagulants because the combined use has been associated with an increased risk of bleeding. Advise patients to inform their healthcare providers if they are taking or planning to take any prescription or over-the-counter medications that increase the risk of bleeding [see Warnings and Precautions (5.7)].

Angle Closure Glaucoma

Advise patients that taking Escitalopram Capsules can cause mild pupillary dilation, which in susceptible individuals, can lead to an episode of angle closure glaucoma [see Warnings and Precautions (5.9)].

Sexual Dysfunction

Advise patients that use of Escitalopram Capsules may cause symptoms of sexual dysfunction in both male and female patients. Inform patients that they should discuss any changes in sexual function and potential management strategies with their healthcare provider [see Warnings and Precautions (5.11)].

Concomitant Medications

Advise patients to inform their physician if they are taking, or plan to take, any prescription or over-the-counter drugs, as there is a potential for interactions. Instruct patients to avoid concomitant use of Escitalopram Capsules and racemic citalopram because escitalopram is the active isomer of racemic citalopram [see Drug Interactions (7)].

Interference with Psychomotor Performance

Because psychoactive drugs may impair judgment, thinking, or motor skills, caution patients about operating hazardous machinery, including automobiles, until they are reasonably certain that Escitalopram Capsules does not affect their ability to engage in such activities [see Warnings and Precautions (5.8)].

Alcohol

Inform patients that the concomitant use of Escitalopram Capsules and alcohol is not recommended [see Drug Interactions (7)].

Pregnancy

Advise pregnant women to notify their healthcare providers if they become pregnant or intend to become pregnant during treatment with Escitalopram Capsules.

Advise patients that Escitalopram Capsules use later in pregnancy may lead to increased risk for neonatal complications requiring prolonged hospitalization, respiratory support, tube feeding, and/or persistent pulmonary hypertension of the newborn [see Use in Specific Populations (8.1)].

Advise women that there is a pregnancy exposure registry that monitors pregnancy outcomes in women exposed to Escitalopram Capsules during pregnancy [see Use in Specific Populations (8.1)].

Lactation

Advise breastfeeding women using Escitalopram Capsules to monitor infants for excess sedation, restlessness, agitation, poor feeding and poor weight gain and to seek medical care if they notice these signs [see Use in Specific Populations (8.2)].

Distributed by:
Almatica Pharma LLC
Morristown, NJ 07960 USA

PI795-00

MEDICATION GUIDE
Escitalopram (es sye tal oh pram) Capsules
for oral use

What is the most important information I should know about Escitalopram Capsules?
Escitalopram Capsules may cause serious side effects, including:

- Increased risk of suicidal thoughts and actions. Escitalopram Capsules and other antidepressant medicines increase the risk of suicidal thoughts and actions in people 24 years of age and younger, especially within the first few months of treatment or when the dose is changed.
  ○ Depression or other mental illnesses are the most important causes of suicidal thoughts or actions.
  How can I watch for and try to prevent suicidal thoughts and actions?
  ○ Pay close attention to any changes, especially sudden changes in mood, behavior, thoughts, or feelings, or if you or your child develop suicidal thoughts or actions. This is very important when an antidepressant medicine is started or when the dose is changed.
  ○ Call your healthcare provider right away to report new or sudden changes in mood, behavior, thoughts, or feelings or if you or your child develop suicidal thoughts or actions.
  ○ Keep all follow-up visits with your healthcare provider as scheduled and call your healthcare provider between visits if you are worried about symptoms.

Call your healthcare provider or get emergency medical help right away if you or your child have any of the following symptoms, especially if they are new, worse, or worry you:

- suicide attempts
- acting aggressive, being angry or violent
- new or worse depression
- panic attacks
- new or worse irritability
- an extreme increase in activity or talking (mania)

- acting on dangerous impulses
- thoughts about suicide or dying
- new or worsening anxiety
- feeling very agitated or restless
- trouble sleeping
- other unusual changes in behavior or mood

What are Escitalopram Capsules?
Escitalopram Capsules are a prescription medicine used to treat:

- a certain type of depression called major depressive disorder (MDD) in adults younger than 65 years of age and children 12 years of age and older
- Generalized anxiety disorder (GAD) in adults younger than 65 years of age.

It is not known if Escitalopram Capsules are safe and effective for use in children under 12 years of age with MDD or if escitalopram is safe and effective for use in children under 7 years of age with GAD.

Who should not take Escitalopram Capsules?
Do not take Escitalopram Capsules if you or your child:

- are taking, or have stopped taking within the last 14 days, a medicine called a monoamine oxidase inhibitor (MAOI), including the antibiotic linezolid or intravenous methylene blue
- are taking the antipsychotic medicine pimozide
- are allergic to escitalopram or citalopram or any of the ingredients in Escitalopram Capsules. See the end of this Medication Guide for a complete list of ingredients in Escitalopram Capsules.

Ask your healthcare provider or pharmacist if you are not sure if you or your child take an MAOI, including the antibiotic linezolid or intravenous methylene blue.
Do not start taking an MAOI for at least 14 days after you or your child have stopped treatment with Escitalopram Capsules.

Before taking Escitalopram Capsules, tell your healthcare provider about all your medical conditions, including if you or your child:

- have or had seizures or convulsions
- have, or have a family history of bipolar disorder, mania, or hypomania
- have low blood sodium levels
- have or had bleeding problems
- have high pressure in the eye (glaucoma)
- have heart, liver, or kidney problems
- are pregnant or plan to become pregnant. Escitalopram Capsules may harm the unborn baby. Taking Escitalopram Capsules during the third trimester of pregnancy may cause the baby to have withdrawal symptoms, or breathing, temperature control, feeding, or other problems after birth. Talk to your healthcare provider about the risks to the baby if you or your child take Escitalopram Capsules during pregnancy.
  ○ Tell your healthcare provider right away if you or your child become pregnant or think you may be pregnant during treatment with Escitalopram Capsules.
  ○ There is a pregnancy registry for females who are exposed to Escitalopram Capsules during pregnancy. The purpose of the registry is to collect information about the health of females exposed to Escitalopram Capsules and their baby. If you or your child become pregnant during treatment with Escitalopram Capsules, talk to your healthcare provider about registering with the National Pregnancy Registry for Antidepressants at 1-844-405-6185 or visit online at https://womensmentalhealth.org/research/pregnancyregistry/antidepressants.
- are breastfeeding or plan to breastfeed. Escitalopram passes into breast milk and may harm the baby. Talk to your healthcare provider about the best way to feed the baby during treatment with Escitalopram Capsules.
  ○ If you or your child breastfeed during treatment with Escitalopram Capsules, call your healthcare provider if the baby develops sleepiness or fussiness, or is not feeding or gaining weight well.

Tell your healthcare provider about all the medicines you or your child take, including prescription and non-prescription medicines, vitamins, and herbal supplements.
Escitalopram Capsules and some medicines may affect each other and may cause serious side effects.
Escitalopram Capsules may affect the way other medicines work and other medicines may affect the way Escitalopram Capsules works.
Especially tell your healthcare provider if you take:

- medicines used to treat migraine headache known as triptans
- tricyclic antidepressants
- lithium
- tramadol, fentanyl, meperidine, methadone, or other opioids
- tryptophan
- buspirone
- amphetamines
- St. John’s Wort
- medicines used to treat mood, anxiety, psychotic or thought disorders, including selective serotonin reuptake inhibitors (SSRIs) and serotonin norepinephrine reuptake inhibitors (SNRIs)
- diuretics
- medicines that can affect blood clotting such as aspirin, nonsteroidal anti-inflammatory drugs (NSAIDs) and warfarin

Ask your healthcare provider if you are not sure if you or your child are taking any of these medicines. Your healthcare provider can tell you if it is safe to take Escitalopram Capsules with your other medicines.
Do not start or stop any other medicines during treatment with Escitalopram Capsules without talking to your healthcare provider first. Stopping Escitalopram Capsules suddenly may cause you or your child to have serious side effects. See “What are the possible side effects of Escitalopram Capsules?”
Know the medicines you or your child take. Keep a list of them to show your healthcare provider and pharmacist when you get new medicine.

How should I take Escitalopram Capsules?

- Take Escitalopram Capsules exactly as your healthcare provider tells you to. Your healthcare provider may need to change the dose of escitalopram until it is the right dose for you or your child. When you first start escitalopram, or if your dose needs to be changed, your healthcare provider will use a different escitalopram medicine.
- Take Escitalopram Capsules 1 time each day, in the morning or the evening.
- Take Escitalopram Capsules with or without food.
- Swallow Escitalopram Capsules whole. Do not open, crush, or chew capsules.
- If you or your child take too much Escitalopram Capsules, call your healthcare provider or Poison Help Line at 1-800-222-1222, or go to the nearest hospital emergency room right away.

What should I avoid while taking Escitalopram Capsules?

- Do not drive, operate heavy machinery, or do other dangerous activities until you know how Escitalopram Capsules affects you. Escitalopram Capsules can cause sleepiness or may affect your ability to make decisions, think clearly, or react quickly.
- You should not drink alcohol during treatment with Escitalopram Capsules.

What are the possible side effects of Escitalopram Capsules?
Escitalopram Capsules may cause serious side effects, including:

- See “What is the most important information I should know about Escitalopram Capsules?”
- Serotonin syndrome. A potentially life-threatening problem called serotonin syndrome can happen when Escitalopram Capsules is taken with certain other medicines. See “Who should not take Escitalopram Capsules?” Call your healthcare provider or go to the nearest hospital emergency room right away if you or your child have any of the following signs and symptoms of serotonin syndrome:

- agitation
- confusion
- fast heartbeat
- sweating
- flushing
- seizures
- nausea, vomiting, diarrhea

- seeing or hearing things that are not real (hallucinations)
- coma
- blood pressure changes
- shaking (tremors), stiff muscles, or muscle twitching
- dizziness
- high body temperature (hyperthermia)
- loss of coordination

- Discontinuation syndrome. Suddenly stopping Escitalopram Capsules may cause you or your child to have serious side effects. Your healthcare provider may want to decrease the escitalopram dose slowly and will switch you to a different escitalopram medicine that is available in a lower dose if you need to stop treatment. Symptoms may include:

- nausea
- sweating
- changes in mood
- irritability and agitation
- dizziness
- electric shock sensation (paresthesia)
- shaking (tremor)
- anxiety

- confusion
- headache
- tiredness
- problems sleeping
- hypomania
- ringing in your ears (tinnitus)
- seizures

- Seizures (convulsions).
- Manic episodes. Manic episodes may happen in people with bipolar disorder who take Escitalopram Capsules. Tell your healthcare provider if you develop any symptoms of mania, which may include:

- greatly increased energy
- racing thoughts
- unusually grand ideas
- talking more or faster than usual

- severe trouble sleeping
- reckless behavior
- excessive happiness or irritability

- Low sodium levels in the blood (hyponatremia). Low sodium levels in the blood that may be serious and may cause death can happen during treatment with Escitalopram Capsules. People who take certain medicines may be at greater risk for developing low sodium levels in the blood. Signs and symptoms may include:

- headache
- weakness or feeling unsteady which can lead to falls
- memory problems

- problems concentrating or thinking
- confusion

In more severe or more sudden cases, signs and symptoms include:

- seeing or hearing things that are not real (hallucinations)
- seizures
- stopping breathing (respiratory arrest)

- fainting
- coma

- Increased risk of bleeding: Taking Escitalopram Capsules with aspirin, NSAIDS, warfarin, or other blood thinners may add to this risk. Tell your healthcare provider if you have any unusual bleeding or bruising.
- Eye problems (angle-closure glaucoma). Escitalopram Capsules may cause a type of eye problem called angle-closure glaucoma in people with certain eye problems. You or your child may want to undergo an eye examination to see if you are at risk and receive preventative treatment if you are. Call your healthcare provider if you or your child have:

- eye pain

- changes in vision

- swelling or redness in or around the eye

- Sexual problems (dysfunction). Taking Escitalopram Capsules may cause sexual problems.
  Symptoms in males may include:

- delayed ejaculation or inability to have an ejaculation
- problems getting or keeping an erection

- decreased sex drive

Symptoms in females may include:

- decreased sex drive

- delayed orgasm or inability to have an orgasm

Talk to your healthcare provider if you develop any changes in your sexual function or if you have any questions or concerns about sexual problems during treatment with Escitalopram Capsules. There may be treatments your healthcare provider can suggest.

The most common side effects of Escitalopram Capsules include:

- trouble sleeping
- delayed ejaculation
- nausea

- increased sweating
- tiredness
- sleepiness

- decreased sex drive
- delayed orgasm or inability to have an orgasm

Height and weight changes in children may happen during treatment with Escitalopram Capsules. Your child’s height and weight should be monitored during treatment with Escitalopram Capsules.
These are not all of the possible side effects of Escitalopram Capsules.
Call your doctor for medical advice about side effects. You may report side effects to FDA at 1-800-FDA-1088.

How should I store Escitalopram Capsules?

- Store Escitalopram Capsules at room temperature between 68°F to 77°F (20°C to 25°C).
- Escitalopram Capsules come in a bottle with a child-resistant cap.
- Keep Escitalopram Capsules and all medicines out of the reach of children.

General information about the safe and effective use of Escitalopram Capsules.
Medicines are sometimes prescribed for purposes other than those listed in a Medication Guide. Do not use Escitalopram Capsules for a condition for which it was not prescribed. Do not give Escitalopram Capsules to other people, even if they have the same symptoms that you have. It may harm them. You may ask your pharmacist or healthcare provider for information about Escitalopram Capsules that is written for health professionals.

What are the ingredients in Escitalopram Capsules?
Active ingredient: escitalopram oxalate
Inactive ingredients: croscarmellose sodium, copovidone, FD&C Blue #1, FD&C Red #40, gelatin, magnesium stearate, microcrystalline cellulose, sodium lauryl sulfate, talc, and titanium dioxide
Distributed by:
Almatica Pharma LLC
Morristown, NJ 07960 USA
For more information about Escitalopram Capsules, call 1-877-447-7979 or visit www.almatica.com.
Additional pediatric use information is approved for AbbVie Inc.’s LEXAPRO (escitalopram) tablets and LEXAPRO (escitalopram) oral solution. However, due to AbbVie Inc.’s marketing exclusivity rights, this drug product is not labeled with that information.

This Medication Guide has been approved by the U.S. Food and Drug Administration.

Issued: 08/2025

MG795-00

PRINCIPAL DISPLAY PANEL

NDC 52427-795-30

Escitalopram Capsules

15 mg

PHARMACIST: Dispense the accompanying Medication Guide to each patient.

30 Capsules

Rx only